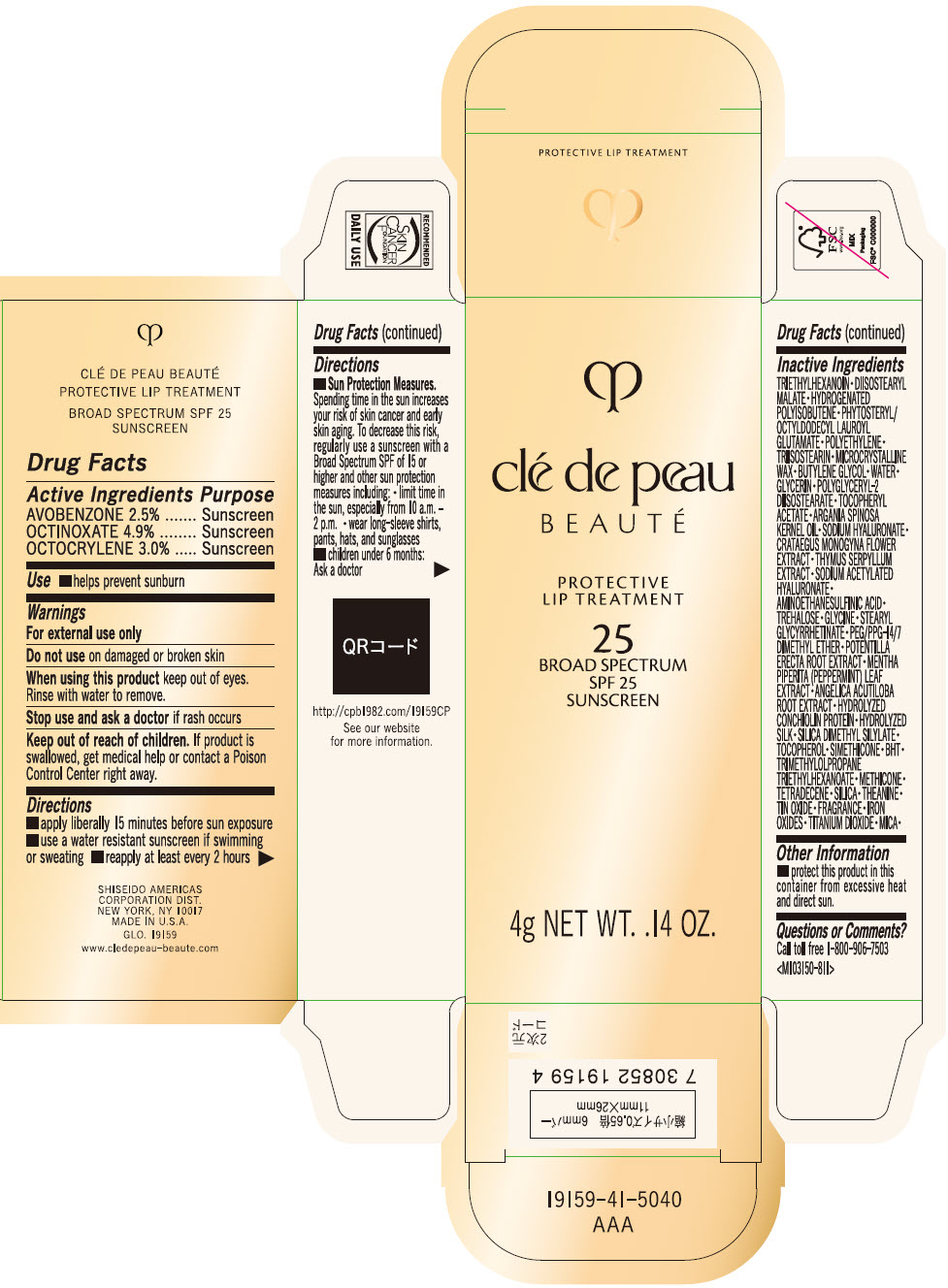 DRUG LABEL: cle de peau BEAUTE PROTECTIVE LIP TREATMENT

NDC: 58411-856 | Form: EMULSION
Manufacturer: SHISEIDO AMERICAS CORPORATION
Category: otc | Type: HUMAN OTC DRUG LABEL
Date: 20260105

ACTIVE INGREDIENTS: AVOBENZONE 100 mg/4 g; OCTINOXATE 196 mg/4 g; OCTOCRYLENE 120 mg/4 g
INACTIVE INGREDIENTS: TRIETHYLHEXANOIN; DIISOSTEARYL MALATE; HYDROGENATED POLYISOBUTENE (1300 MW); PHYTOSTERYL/OCTYLDODECYL LAUROYL GLUTAMATE; HIGH DENSITY POLYETHYLENE; TRIISOSTEARIN; MICROCRYSTALLINE WAX; BUTYLENE GLYCOL; WATER; GLYCERIN; POLYGLYCERYL-2 DIISOSTEARATE; .ALPHA.-TOCOPHEROL ACETATE; ARGAN OIL; HYALURONATE SODIUM; CRATAEGUS MONOGYNA FLOWER; THYMUS SERPYLLUM WHOLE; SODIUM ACETYLATED HYALURONATE; HYPOTAURINE; TREHALOSE; GLYCINE; STEARYL GLYCYRRHETINATE; PEG/PPG-14/7 DIMETHYL ETHER; POTENTILLA ERECTA ROOT; MENTHA PIPERITA LEAF; ANGELICA ACUTILOBA ROOT; SILICA DIMETHYL SILYLATE; TOCOPHEROL; BUTYLATED HYDROXYTOLUENE; TRIMETHYLOLPROPANE TRIETHYLHEXANOATE; METHICONE (20 CST); 1-TETRADECENE; SILICON DIOXIDE; THEANINE; STANNIC OXIDE; FERRIC OXIDE RED; TITANIUM DIOXIDE; MICA

clé de peau BEAUTÉ PROTECTIVE LIP TREATMENT
SPF 25

Drug Facts

ACTIVE INGREDIENT

Active ingredients | Purpose
AVOBENZONE 2.5% | Sunscreen
OCTINOXATE 4.9% | Sunscreen
OCTOCRYLENE 3.0% | Sunscreen

Uses

- helps prevent sunburn

Warnings

For external use only

Do not useon damaged or broken skin

WHEN USING

When using this productkeep out of eyes. Rinse with water to remove.

Stop use and ask a doctorif rash occurs

Keep out of reach of children.If product is swallowed, get medical help or contact a Poison Control Center right away.

Directions

For sunscreen use:

- apply liberally 15 minutes before sun exposure
- use a water resistant sunscreen if swimming or sweating
- reapply at least every 2 hours
- Sun Protection Measures. Spending time in the sun increases your risk of skin cancer and early skin aging. To decrease this risk, regularly use a sunscreen with a Broad Spectrum SPF of 15 or higher and other sun protection measures including:
  - limit time in the sun, especially from 10 a.m. – 2 p.m.
  - wear long-sleeve shirts, pants, hats, and sunglasses
- children under 6 months: Ask a doctor

Inactive Ingredients

TRIETHYLHEXANOIN ▪ DIISOSTEARYL MALATE ▪ HYDROGENATED POLYISOBUTENE ▪ PHYTOSTERYL/OCTYLDODECYL LAUROYL GLUTAMATE ▪ POLYETHYLENE ▪ TRIISOSTEARIN ▪ MICROCRYSTALLINE WAX ▪ BUTYLENE GLYCOL ▪ WATER ▪ GLYCERIN ▪ POLYGLYCERYL-2 DIISOSTEARATE ▪ TOCOPHERYL ACETATE ▪ ARGANIA SPINOSA KERNEL OIL ▪ SODIUM HYALURNATE ▪ CRATAEGUS MONOGYNA FLOWER EXTRACT ▪ THYMUS SERPYLLUM EXTRACT ▪ SODIUM ACETYLATED HYALURONATE ▪ AMINOETHANESULFINIC ACID ▪ TREHALOSE ▪ GLYCINE ▪ STEARYL GLYCYRRHETINATE ▪ PEG/PPG-14/7 DIMETHYL ETHER ▪ POTENTILLA ERECTA ROOT EXTRACT ▪ MENTHA PIPERITA (PEPPERMINT) LEAF EXTRACT ▪ ANGELICA ACUTILOBA ROOT EXTRACT ▪ HYDROLYZED CONCHIOLIN PROTEIN ▪ HYDROLYZED SILK ▪ SILICA DIMETHYL SILYLATE ▪ TOCOPHEROL ▪ SIMETHICONE ▪ BHT ▪ TRIMETHYLOLPROPANE TRIETHYLHEXANOATE ▪ METHICONE ▪ TETRADECENE ▪ SILICA ▪ THEANINE ▪ TIN OXIDE ▪ FRAGRANCE ▪ IRON OXIDES ▪ TITANIUM DIOXIDE ▪ MICA ▪

Other information

- protect this product in this container from excessive heat and direct sun.

Questions or Comments?

Call toll free 1-800-906-7503

PRINCIPAL DISPLAY PANEL - 4 g Bottle Box

clé de peau
BEAUTÉ

PROTECTIVE
LIP TREATMENT

25
BROAD SPECTRUM
SPF 25
SUNSCREEN

4g NET WT. .14 OZ.